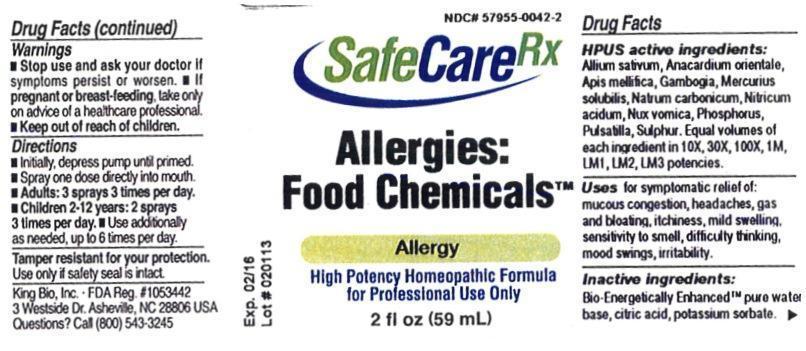 DRUG LABEL: Allergies Food Chemicals
NDC: 57955-0042 | Form: LIQUID
Manufacturer: King Bio Inc.
Category: homeopathic | Type: HUMAN PRESCRIPTION DRUG LABEL
Date: 20130417

ACTIVE INGREDIENTS: GARLIC 10 [hp_X]/59 mL; SEMECARPUS ANACARDIUM JUICE 10 [hp_X]/59 mL; APIS MELLIFERA 10 [hp_X]/59 mL; GAMBOGE 10 [hp_X]/59 mL; MERCURIUS SOLUBILIS 10 [hp_X]/59 mL; SODIUM CARBONATE 10 [hp_X]/59 mL; NITRIC ACID 10 [hp_X]/59 mL; STRYCHNOS NUX-VOMICA SEED 10 [hp_X]/59 mL; PHOSPHORUS 10 [hp_X]/59 mL; PULSATILLA VULGARIS 10 [hp_X]/59 mL; SULFUR 10 [hp_X]/59 mL
INACTIVE INGREDIENTS: WATER; CITRIC ACID MONOHYDRATE; POTASSIUM SORBATE

Allergies Food Chemicals

Warnings

- Stop use and ask you doctor if symptoms persist or worsen.
- If pregnant or breast-feeding, take only on advice of a healthcare professional.
- Keep out of reach of children.

Tamper resistant for your protection. Use only if safety seal is intact.

Keep out of reach of children.

Directions

- Initially, depress pump until primed.
- Spray one dose directly into mouth.
- Adults: 3 sprays 3 times per day.
- Children 2-12 years: 2 sprays 3 times per day.
- Use Additionally as needed, up to 6 times per day.

HPUS Active Ingredients:

Allium sativum, Anacardium orientale, Apis mellifica, Gambogia, Mercurius solubilis, Natrum carbonicum, Nitricum acidum, Nux vomica, Phosphorus, Pulsatilla, Sulphur. Equal volumes of each ingredient in 10X, 30X, 100X, 1M, LM1, LM2, LM3 potencies.

Indications and Usage

Uses for symptomatic relief of: mucous congestion, headaches, gas and bloating, itchiness, mild swelling, sensitivity to smell, difficulty thinking, mood swings, irritability.

Inactive Ingredients

Bio-Energetically Enhanced™ pure water base, citric acid, potassium sorbate.

Purpose

Uses for symptomatic relief of:

- mucous congestion
- headaches
- gas and bloating
- itchiness
- mild swelling
- sensitivity to smell
- difficulty thinking
- mood swings
- irritability